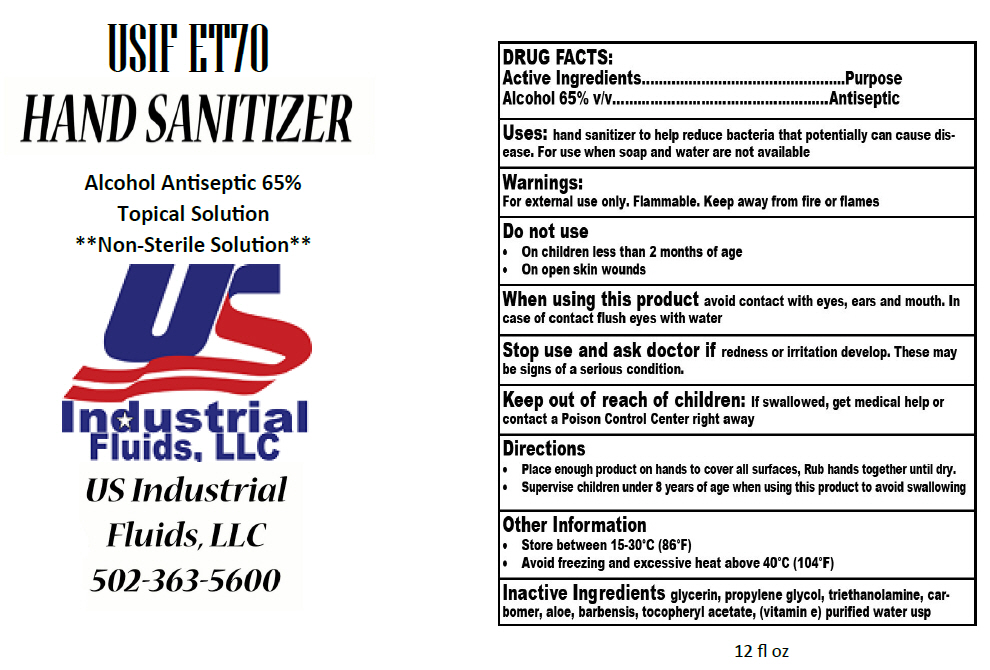 DRUG LABEL: USIF 
NDC: 77439-070 | Form: GEL
Manufacturer: US Industrial Fluids,LLC
Category: otc | Type: HUMAN OTC DRUG LABEL
Date: 20200521

ACTIVE INGREDIENTS: Alcohol 65 mL/100 mL
INACTIVE INGREDIENTS: WATER; GLYCERIN; Aloe; .ALPHA.-TOCOPHEROL ACETATE; TROLAMINE; CARBOMER HOMOPOLYMER, UNSPECIFIED TYPE

USIF
ET 70

DRUG FACTS:

Active Ingredients

Alcohol 65% v/v

Purpose

Antiseptic

Uses

hand sanitizer to help reduce bacteria that potentially can cause disease. For use when soap and water are not available

Warnings

For external use only. Flammable. Keep away from fire or flames

Do not use

- On children less than 2 months of age
- On open skin wounds

When using this product avoid contact with eyes, ears and mouth. In case of contact flush eyes with water

Stop use and ask doctor if redness or irritation develop. These may be signs of a serious condition.

Keep out of reach of children

If swallowed, get medical help or contact a Poison Control Center right away

Directions

- Place enough product on hands to cover all surfaces, Rub hands together until dry.
- Supervise children under 8 years of age when using this product to avoid swallowing

Other Information

- Store between 15-30°C (86°F)
- Avoid freezing and excessive heat above 40°C (104°F)

Inactive Ingredients

glycerin, propylene glycol, triethanolamine, carbomer, aloe, barbensis, tocopheryl acetate, (vitamin e) purified water usp

PRINCIPAL DISPLAY PANEL - 12 fl oz Bottle Label

USIF ET70
HAND SANITIZER

Alcohol Antiseptic 65%
Topical Solution
**Non-Sterile Solution**

US Industrial
Fluids, LLC
502-363-5600